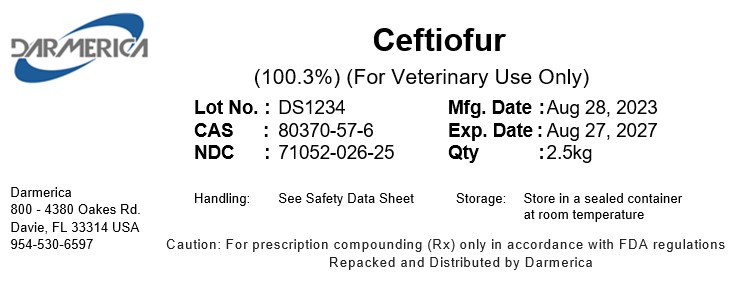 DRUG LABEL: Ceftiofur
NDC: 71052-026 | Form: POWDER
Manufacturer: DARMERICA, LLC
Category: other | Type: BULK INGREDIENT - ANIMAL DRUG
Date: 20241219

ACTIVE INGREDIENTS: CEFTIOFUR 1 kg/1 kg

Ceftiofur